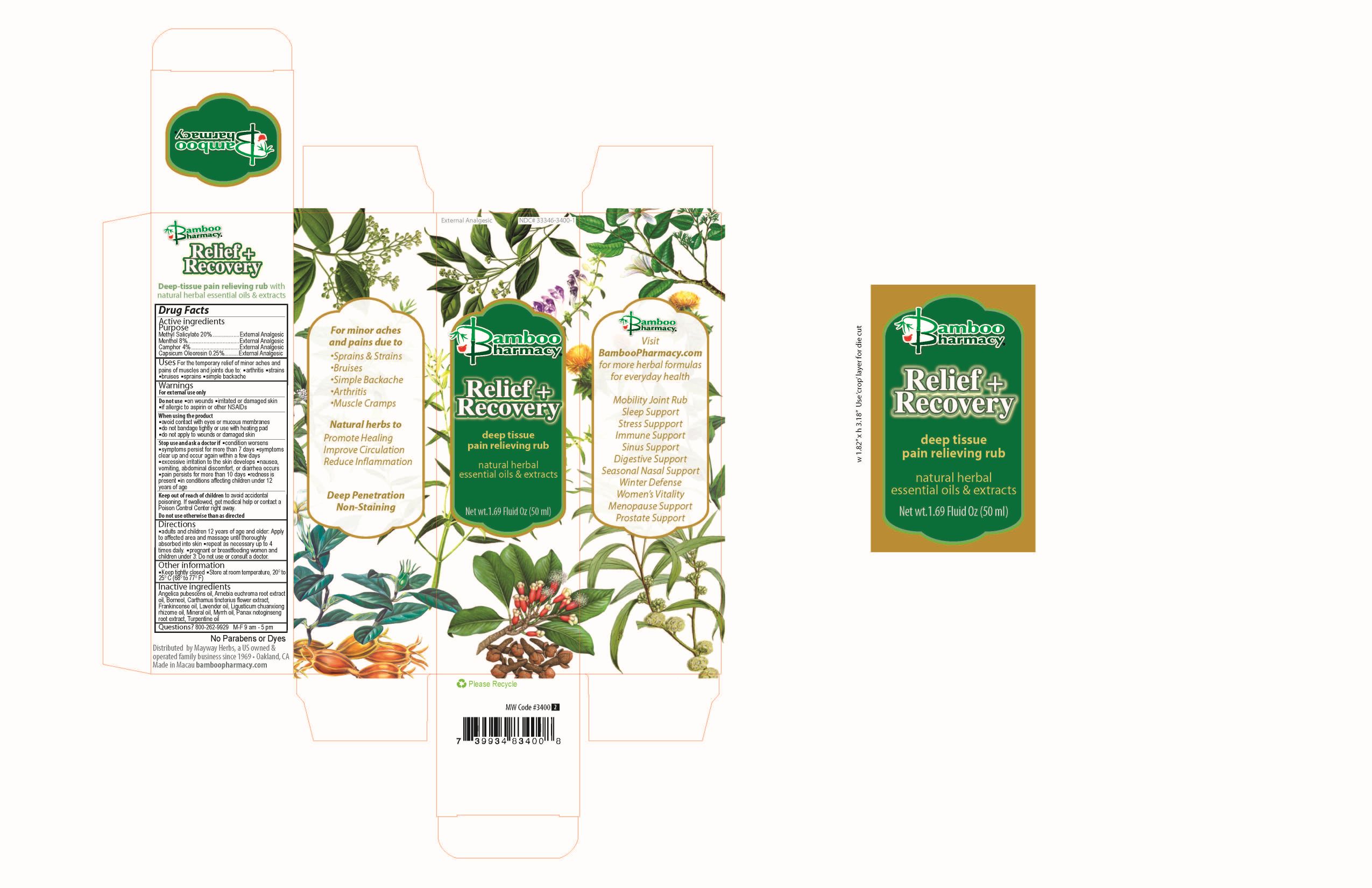 DRUG LABEL: Relief Recovery
NDC: 33346-3400 | Form: OIL
Manufacturer: Mayway Corporation
Category: otc | Type: HUMAN OTC DRUG LABEL
Date: 20251223

ACTIVE INGREDIENTS: METHYL SALICYLATE 20 g/50 mL; MENTHOL 8 g/50 mL; CAMPHOR OIL 4 g/50 mL; CAPSICUM OLEORESIN 0.25 g/50 mL
INACTIVE INGREDIENTS: BORNEOL; TURPENTINE OIL; LAVENDER OIL; PANAX NOTOGINSENG ROOT; CARTHAMUS TINCTORIUS FLOWER OIL; ANGELICA PUBESCENS WHOLE; LIGUSTICUM SINENSE SUBSP. CHUANXIONG WHOLE; FRANKINCENSE OIL; MYRRH OIL; ARNEBIA EUCHROMA ROOT; MINERAL OIL

Relief+Recovery

Active ingredients

Methyl salicylate 20%......……….…….External analgesic
Menthol 8%.....................……….…….External analgesic
Camphor 4%...................……….…….External analgesic
Capsicum oleoresin 0.25%......…….External analgesic

Do not use otherwise than as directed

Keep out of reach of children to avoid accidental poisoning.

If swallowed, get medical help or contact a Poison Control Center right away

Do not use otherwise than as directed

Directions

Pregnant or breastfeeding women and children under 3: Do not use of consult a doctor

Directions

- adults and children 12 years of age and older: Apply generously to the affected area and massage until thoroughly absorbed into skin

- repeat as necessary but not more than 4 times daily.

- pregnant or breastfeeding women and children under 3: Do not use of consult a doctor

Other information

- Keep tightly closed
- Store at room temperature, 20° to 25°C(68° to 77F)

Inactive ingredients

Angelica Pubescens oil, Arnebia euchroma root extract oil, Borneol, Carthamus tinctorius flower extract, Frankincense oil, Lavender oil, Ligusticum chuanxiong zhizome oil, Mineral Oil, Myrrh oil, Panax notoginseng root extract, Turpentine oil

Questions?

+1-800-262-9929 M-F 9am - 5pm

Warnings

For external use only

Purpose

External analgesic

Do not use

- on wounds
- irritated or damaged skin
- if allergic to aspirin or other NSAIDs

When using this product

- avoid contact with the eyes or mucous membranes
- do not bandage tightly or use with heating pad
- do not apply to wounds or damaged skin

Stop use and ask a doctor if

- condition worsens
- symptoms persist for more than 7 days
- symptoms clear up and occur again within a few days
- excessive irritation of the skin develops
- nausea, vomiting, abdominal discomfort, or diarrhea occurs
- pain persists for more than 10 days
- redness is present
- in conditions affecting children under 12 years of age

Warnings

For external use only

Uses

For the temporary relief of minor aches and pains of muscles and joints due to:

- arthritis
- strains
- bruises
- sprains
- simple backache

Relief + Recovery Principal Display Panel